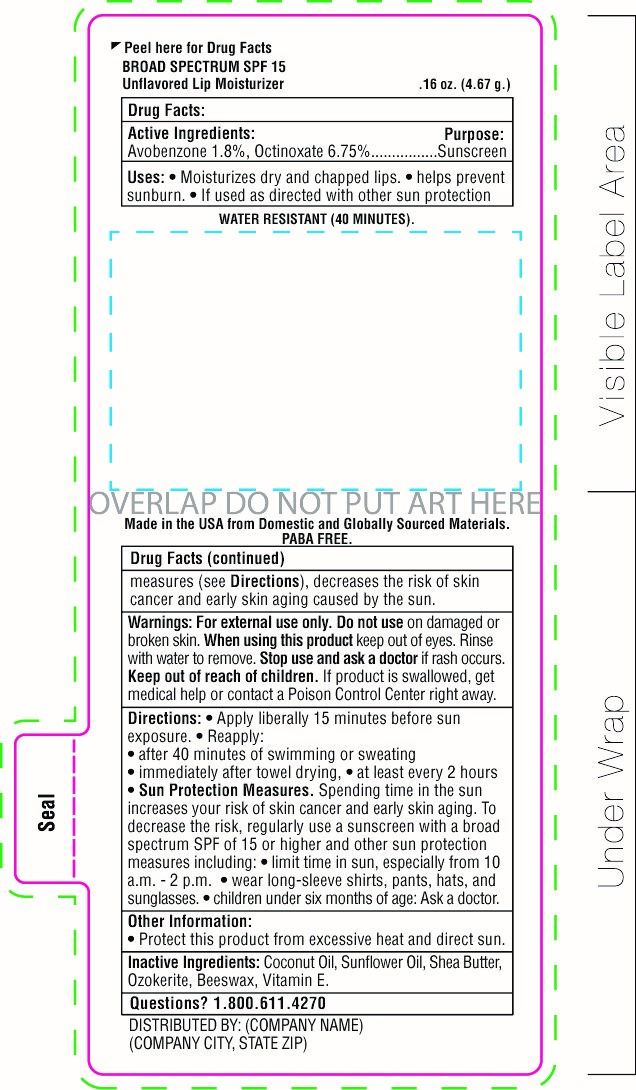 DRUG LABEL: SnugZ SPF 15 Beeswax Lip Balm
NDC: 76309-200 | Form: STICK
Manufacturer: SnugZ/USA, LLC
Category: otc | Type: HUMAN OTC DRUG LABEL
Date: 20251229

ACTIVE INGREDIENTS: AVOBENZONE 0.09 g/4.67 g; OCTINOXATE 0.35 g/4.67 g
INACTIVE INGREDIENTS: WHITE WAX

ZLBP - SPF 15 Lip Balm